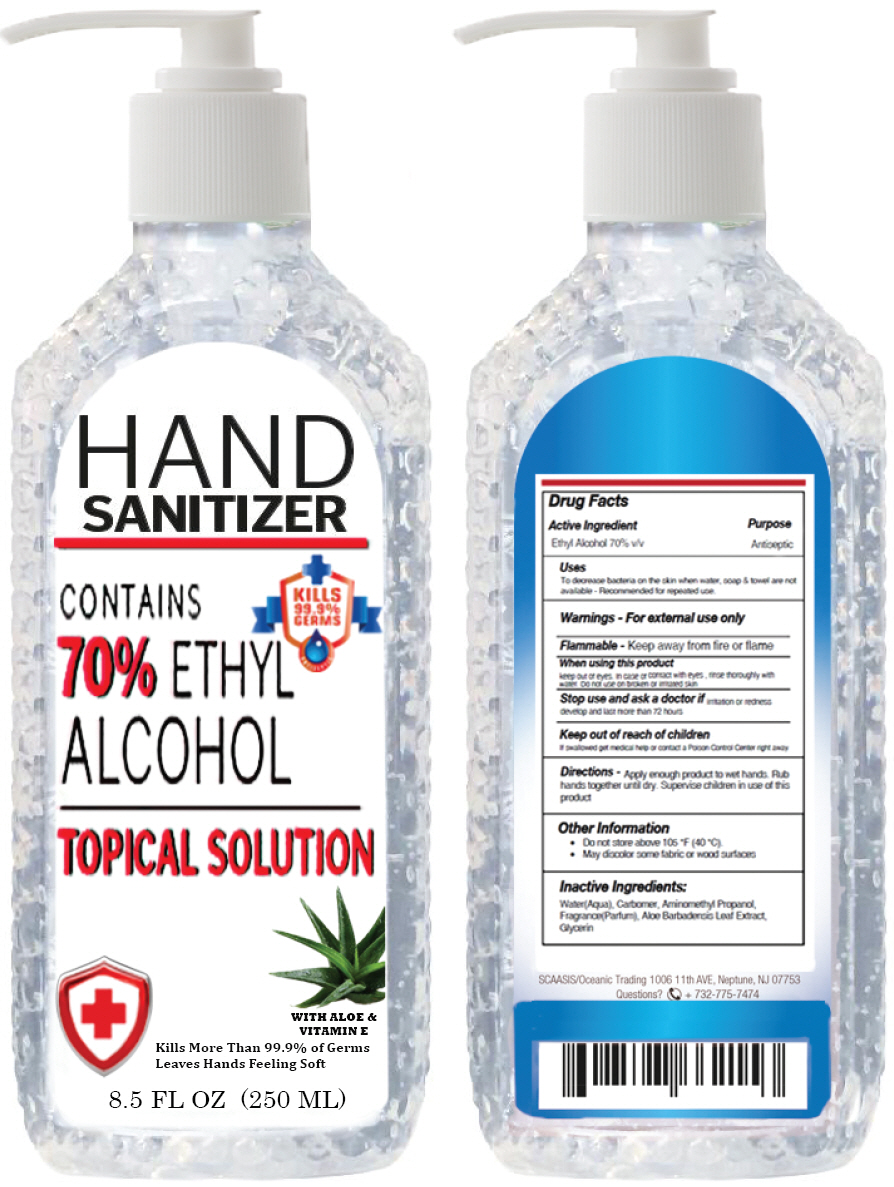 DRUG LABEL: HAND SANITIZER
NDC: 75624-123 | Form: GEL
Manufacturer: SCAASIS ORIGINALS INC
Category: otc | Type: HUMAN OTC DRUG LABEL
Date: 20200526

ACTIVE INGREDIENTS: ALCOHOL 70 mL/100 mL
INACTIVE INGREDIENTS: WATER; CARBOMER HOMOPOLYMER, UNSPECIFIED TYPE; AMINOMETHYLPROPANOL; GLYCERIN; PROPYLENE GLYCOL; FRAGRANCE LAVENDER & CHIA F-153480; ALOE VERA LEAF

HAND SANITIZER

Drug Facts

Active Ingredient

Ethyl Alcohol 70% v/v

Purpose

Antiseptic

Uses

To decrease bacteria on the skin when water, soap & towel are not available - Recommended for repeated use.

Warnings

For external use only

Flammable - Keep away from fire or flame

When using this product keep out of eyes. In case of contact with eyes , rinse thoroughly with water. Do not use on broken or irritated skin

Stop use and ask a doctor if irritation or redness develop and last more than 72 hours

Keep out of reach of children

If swallowed get medical help or contact a Poison Control Center right away

Directions

Apply enough product to wet hands. Rub hands together until dry. Supervise children in use of this product

Other Information

- Do not store above 105 *F (40 *C).
- May discolor some fabric or wood surfaces

Inactive Ingredients

Water(Aqua), Carbomer, Aminomethyl Propanol, Fragrance(Parfum), Aloe Barbadensis Leaf Extract, Glycerin

Questions?

+ 732-775-7474

PRINCIPAL DISPLAY PANEL - 250 ML Bottle Label

HAND
SANITIZER

KILLS
99.9%
GERMS

CONTAINS
70% ETHYL
ALCOHOL

TOPICAL SOLUTION

WITH ALOE &
VITAMIN E

Kills More Than 99.9% of Germs
Leaves Hands Feeling Soft

8.5 FL OZ (250 ML)